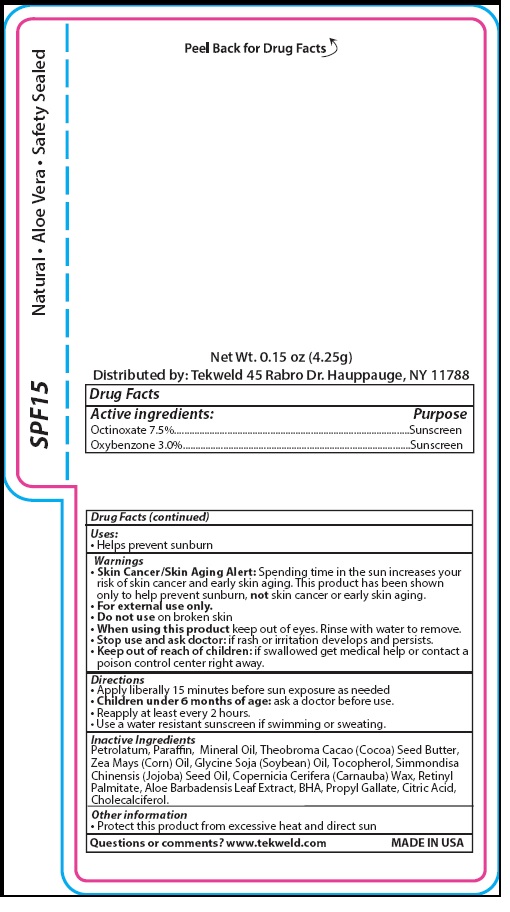 DRUG LABEL: CB 102
NDC: 71160-192 | Form: LIPSTICK
Manufacturer: Tekweld Solutions, Inc.
Category: otc | Type: HUMAN OTC DRUG LABEL
Date: 20190409

ACTIVE INGREDIENTS: OCTINOXATE 0.31875 g/4.25 g; OXYBENZONE 0.1275 g/4.25 g
INACTIVE INGREDIENTS: PETROLATUM; PARAFFIN; MINERAL OIL; COCOA BUTTER; CORN OIL; SOYBEAN OIL; TOCOPHEROL; JOJOBA OIL; CARNAUBA WAX; VITAMIN A PALMITATE; ALOE VERA LEAF; BUTYLATED HYDROXYANISOLE; PROPYL GALLATE; CITRIC ACID MONOHYDRATE; CHOLECALCIFEROL

SPF 15

Drug Facts

Active ingredients:
Octinoxate 7.5%
Oxybenzone 3.0%

Purpose:
Octinoxate ..............................Sunscreen
Oxybenzone ...........................Sunscreen

Uses:

- Helps prevent sunburn

Warnings

• Skin Cancer/Skin Aging Alert: Spending time in the sun increases your
risk of skin cancer and early skin aging. This product has been shown
only to help prevent sunburn, not skin cancer or early skin aging.

OTHER SAFETY INFORMATION

• For external use only.

• Do not use on broken skin

• When using this product keep out of eyes. Rinse with water to remove.

• Stop use and ask doctor: if rash or irritation develops and persists.

• Keep out of reach of children. If swallowed, get medical help or contact a Poison Control Center right away.

Directions
• Apply liberally 15 minutes before sun exposure as needed
• Children under 6 months of age: ask a doctor before use.
• Reapply at least every 2 hours.
• Use a water resistant sunscreen if swimming or sweating.

Inactive Ingredients
Petrolatum, Paraffin, Mineral Oil, Theobroma Cacao (Cocoa) Seed Butter,
Zea Mays (Corn) Oil, Glycine Soja (Soybean) Oil, Tocopherol, Simmondisa
Chinensis (Jojoba) Seed Oil, Copernicia Cerifera (Carnauba) Wax, Retinyl
Palmitate, Aloe Barbadensis Leaf Extract, BHA, Propyl Gallate, Citric Acid,
Cholecalciferol.

Other information
• Protect this product from excessive heat and direct sun

Questions or comments? www.tekweld.com MADE IN USA

Product Package

SPF15 Natural • Aloe Vera • Safety Sealed

Peel Back for Drug Facts

Net Wt. 0.15 oz (4.25g)
Distributed by: Tekweld 45 Rabro Dr. Hauppauge, NY 11788

res